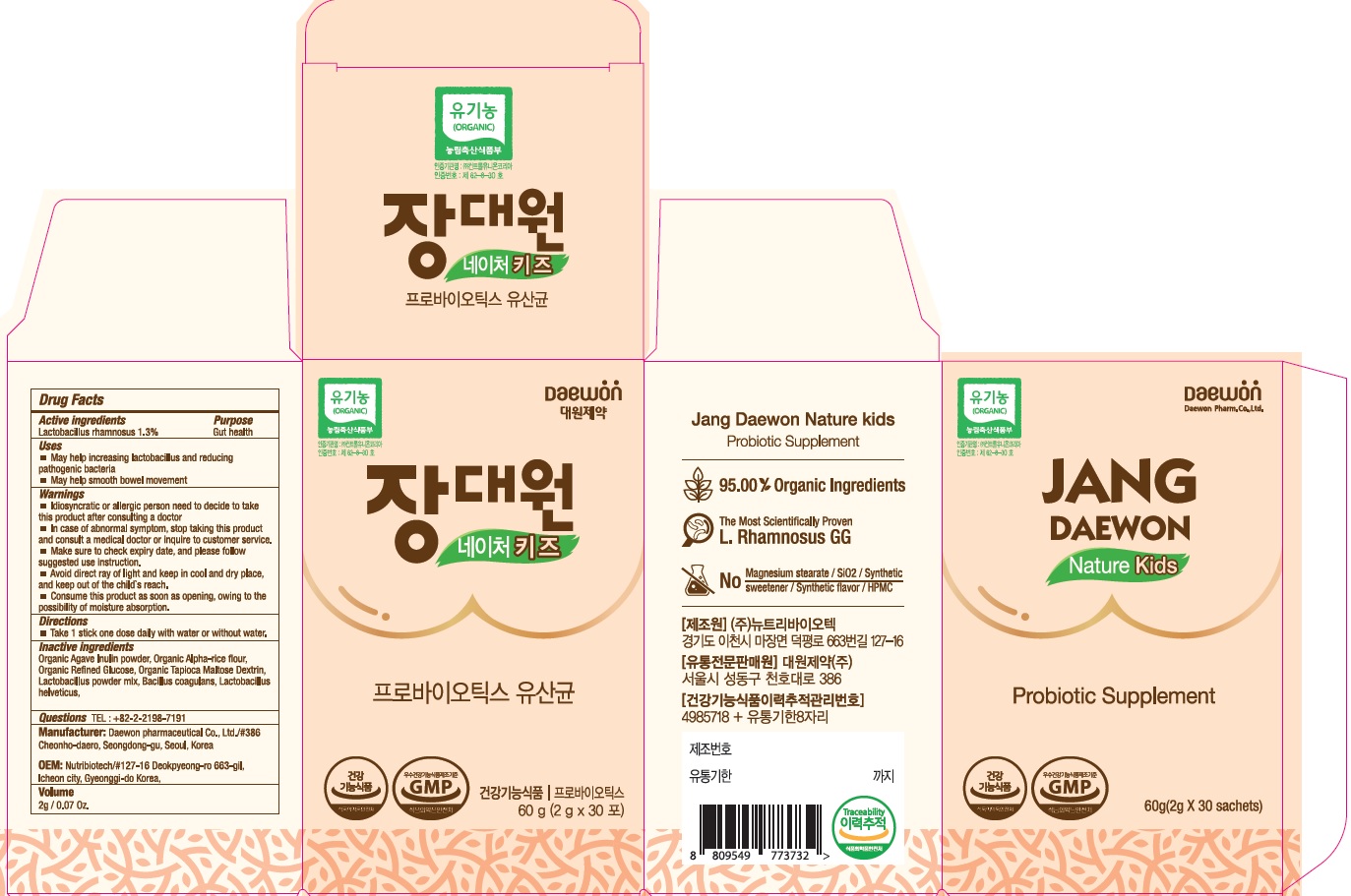 DRUG LABEL: Jangdaewon Nature Plus
NDC: 72460-500 | Form: POWDER
Manufacturer: Daewon Pharmaceutical Co., Ltd.
Category: otc | Type: HUMAN OTC DRUG LABEL
Date: 20190313

ACTIVE INGREDIENTS: Lactobacillus rhamnosus 22.5 mg/3 g
INACTIVE INGREDIENTS: Lactobacillus helveticus

ACTIVE INGREDIENT

Active ingredients: Lactobacillus rhamnosus 0.75%

INACTIVE INGREDIENT

Inactive ingredients:

Organic Agave Inulin powder, Organic Alpha-rice flour, Organic Refined Glucose, Organic Tapioca Maltose Dextrin, Lactobacillus powder mix, Dried yeast (active, Saccharomyces boulardii), Lactobacillus helveticus, Bifidobacterium bifidum

PURPOSE

Purpose: Gut health

WARNINGS

■ Idiosyncratic or allergic person need to decide to take this product after consulting a doctor
■ In case of abnormal symptom, stop taking this product and consult a medical doctor or inquire to customer service.
■ Make sure to check expiry date, and please follow suggested use instruction.
■ Avoid direct ray of light and keep in cool and dry place, and keep out of the child's reach.
■ Consume this product as soon as opening, owing to the possibility of moisture absorption.

KEEP OUT OF REACH OF CHILDREN

Keep out of the child's reach.

Uses

■ May help increasing lactobacillus and reducing pathogenic bacteria
■ May help smooth bowel movement

Directions

■ Take 1 stick one dose daily with water or without water.